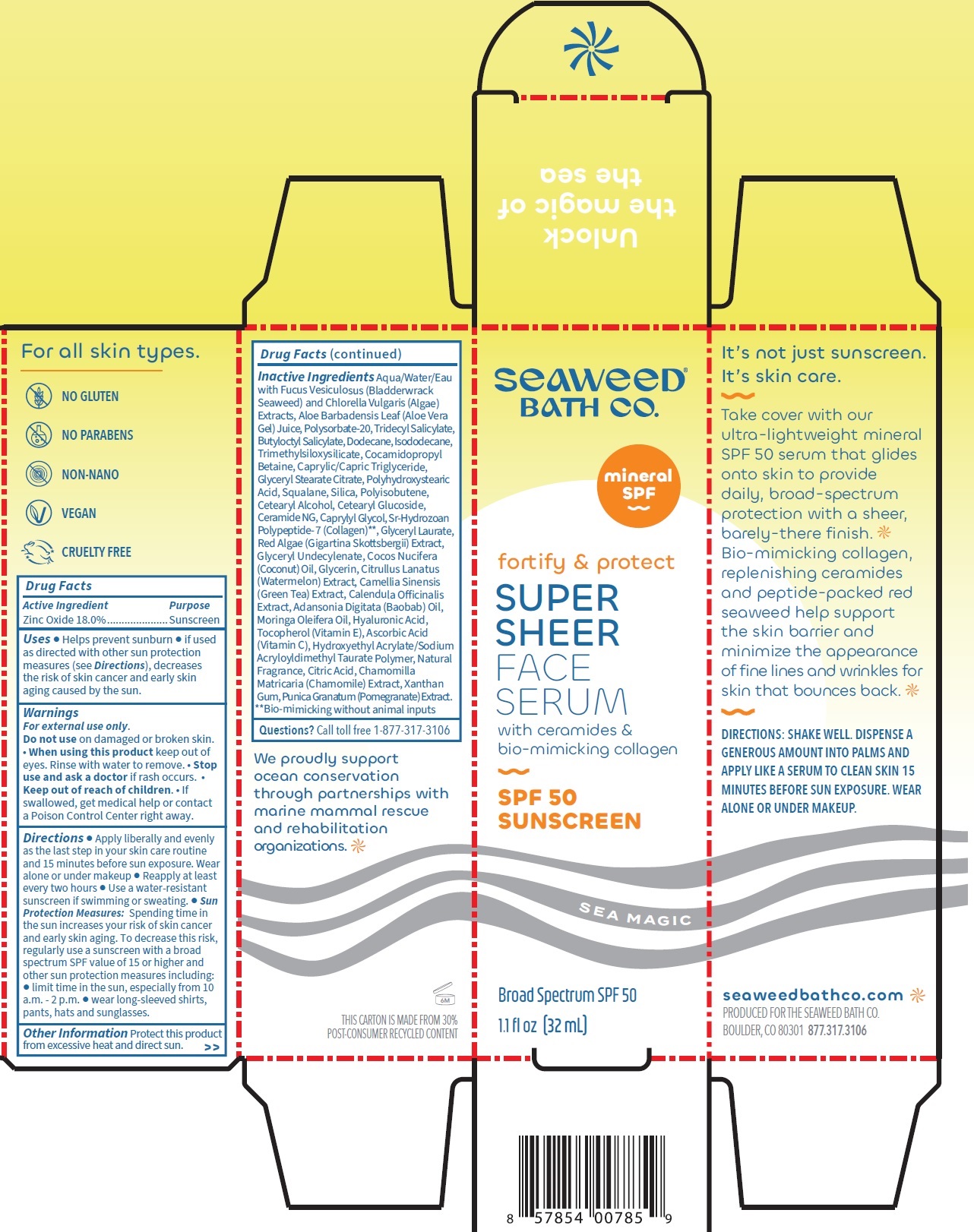 DRUG LABEL: SEAWEED BATH CO. Super Sheer Face Serum SPF-50
NDC: 81159-388 | Form: SOLUTION
Manufacturer: The Seaweed Bath Co.
Category: otc | Type: HUMAN OTC DRUG LABEL
Date: 20250128

ACTIVE INGREDIENTS: ZINC OXIDE 180 mg/1 mL
INACTIVE INGREDIENTS: WATER; CHLORELLA VULGARIS; ALOE VERA LEAF; POLYSORBATE 20; TRIDECYL SALICYLATE; BUTYLOCTYL SALICYLATE; DODECANE; ISODODECANE; COCAMIDOPROPYL BETAINE; MEDIUM-CHAIN TRIGLYCERIDES; GLYCERYL STEARATE CITRATE; SQUALANE; SILICON DIOXIDE; CETOSTEARYL ALCOHOL; CETEARYL GLUCOSIDE; CERAMIDE NG; CAPRYLYL GLYCOL; GLYCERYL LAURATE; GIGARTINA SKOTTSBERGII; COCONUT OIL; GLYCERIN; WATERMELON; GREEN TEA LEAF; CALENDULA OFFICINALIS FLOWER; ADANSONIA DIGITATA SEED OIL; HYALURONIC ACID; TOCOPHEROL; ASCORBIC ACID; CITRIC ACID MONOHYDRATE; CHAMOMILE; XANTHAN GUM; PUNICA GRANATUM ROOT BARK

SEAWEED BATH CO. Super Sheer Face Serum SPF-50

Active Ingredient

Zinc Oxide 18.0%

Purpose

Sunscreen

Uses

• Helps prevent sunburn • if used as directed with other sun protection measures (see), decreases the risk of skin cancer and early skin aging caused by the sun. Directions

Warnings

For external use only.

Do not use

on damaged or broken skin.

When using this product

- keep out of eyes. Rinse with water to remove.

Stop use and ask a doctor

- if rash occurs.

Keep out of reach of children.

• If swallowed, get medical help or contact a Poison Control Center right away.

Directions

• Apply liberally and evenly as the last step in your skin care routine and 15 minutes before sun exposure. Wear alone or under makeup • Reapply at least every two hours • Use a water-resistant sunscreen if swimming or sweating. • Spending time in the sun increases your risk of skin cancer and early skin aging. To decrease this risk, regularly use a sunscreen with a broad spectrum SPF value of 15 or higher and other sun protection measures including: • limit time in the sun, especially from 10 a.m. - 2 p.m. • wear long-sleeved shirts, pants, hats and sunglasses. Sun Protection Measures:

Other Information

Protect this product from excessive heat and direct sun.

Inactive Ingredients

Aqua/Water/Eau with Fucus Vesiculosus (Bladderwrack Seaweed) and Chlorella Vulgaris (Algae) Extracts, Aloe Barbadensis Leaf (Aloe Vera Gel) Juice, Polysorbate-20, Tridecyl Salicylate, Butyloctyl Salicylate, Dodecane, Isododecane, Trimethylsiloxysilicate, Cocamidopropyl Betaine, Caprylic/Capric Triglyceride, Glyceryl Stearate Citrate, Polyhydroxystearic Acid, Squalane, Silica, Polyisobutene, Cetearyl Alcohol, Cetearyl Glucoside, Ceramide NG, Caprylyl Glycol, Sr-Hydrozoan Polypeptide- 7 (Collagen)**, Glyceryl Laurate, Red Algae (Gigartina Skottsbergii) Extract, Glyceryl Undecylenate, Cocos Nucifera (Coconut) Oil, Glycerin, Citrullus Lanatus (Watermelon) Extract, Camellia Sinensis (Green Tea) Extract, Calendula officianalis Extract, Adansonia Digitata (Baobab) Oil, Moringa Oleifera Oil, Hyaluronic Acid, Tocopherol (Vitamin E), Ascorbic Acid (Vitamin C), Hydroxyethyl Acrylate/Sodium Acryloyldimethyl Taurate Polymer, Natural Fragrance, Citric Acid, Chamomilla Matricaria (Chamomile) Extract, Xanthan Gum, Punica Granatum (Pomegranate) Extract. **Bio-mimicking without animal inputs

Questions?

Call toll free 1-877-317-3106